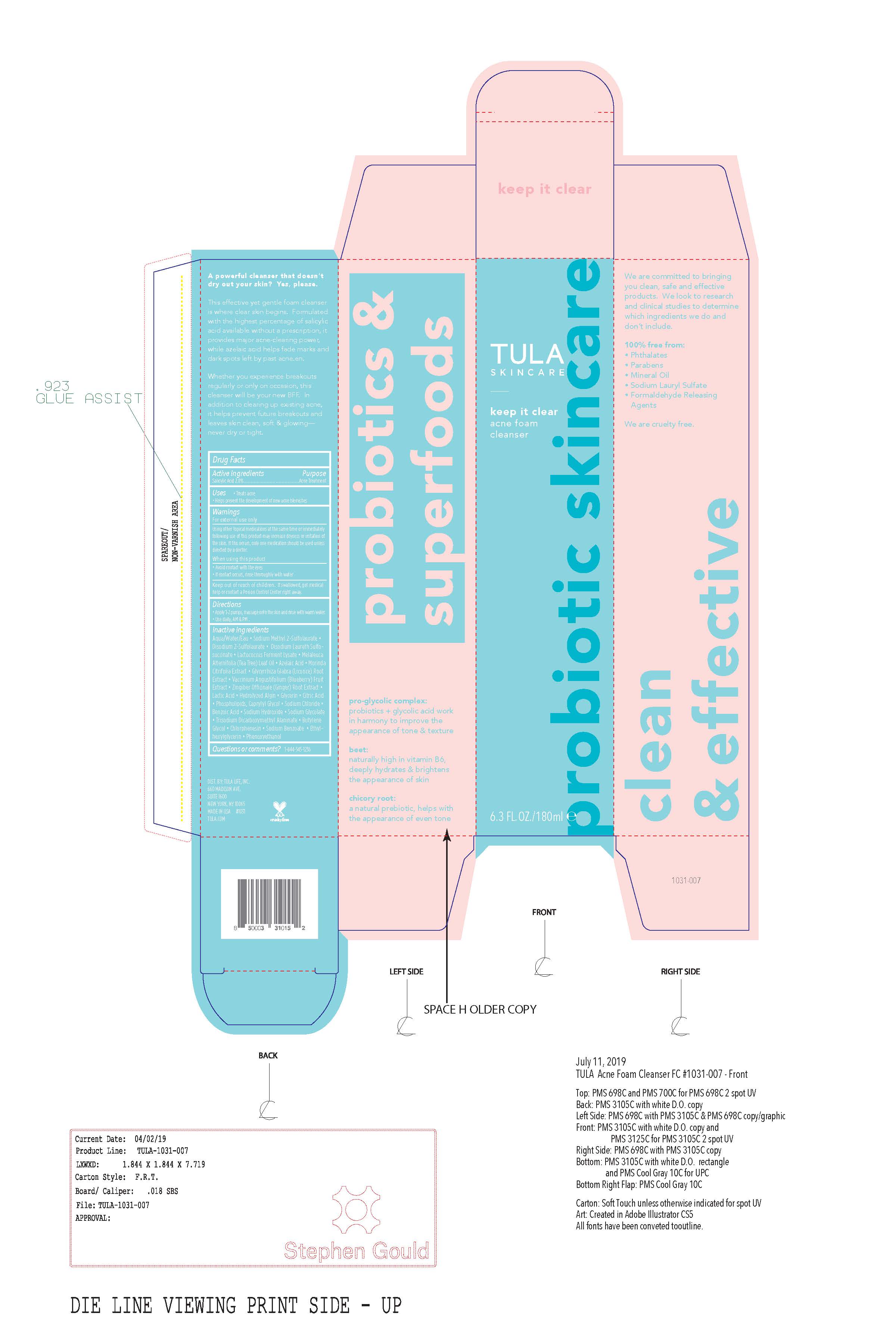 DRUG LABEL: KEEP IT CLEAR ACNE FOAM CLEANSER
NDC: 59735-440 | Form: CREAM
Manufacturer: MANA PRODUCTS,INC.
Category: otc | Type: HUMAN OTC DRUG LABEL
Date: 20240822

ACTIVE INGREDIENTS: SALICYLIC ACID 2 g/100 g
INACTIVE INGREDIENTS: DIMETHYL ISOSORBIDE; POLYSORBATE 20; AZELAIC ACID; .ALPHA.-BISABOLOL, (+)-; CETEARYL OLIVATE; CITRULLUS LANATUS WHOLE; EPILOBIUM ANGUSTIFOLIUM WHOLE; LACTIC ACID; ORYZA SATIVA WHOLE; ALOE VERA LEAF; DIMETHICONE; NIACINAMIDE; WATER; GLYCERIN; LACTOCOCCUS LACTIS; SACCHARIDE ISOMERATE; SORBITAN ISOSTEARATE; ETHYLHEXYLGLYCERIN; PROPANEDIOL; CITRUS AURANTIUM FLOWER; HYDROXYETHYL ACRYLATE/SODIUM ACRYLOYLDIMETHYL TAURATE COPOLYMER (100000 MPA.S AT 1.5%); PHENOXYETHANOL; SODIUM CHLORIDE; SODIUM LACTATE; SORBITAN OLIVATE; TRISODIUM ETHYLENEDIAMINE DISUCCINATE; XANTHAN GUM; BLUEBERRY

TUL ACNE FOAM CLEANSER

ACTIVE INGREDIENTS

Salicylic Acid 2.0%

PURPOSE

Acne Treatment

USES

- treats acne

• Helps prevent the development or new acne blemishes

WARNINGS

For external use only
Using other topical medications at the same time or
immediately following use of this product may increase
dryness or irritation of the skin. If this occurs, only one
medication should be used unless directed by a doctor.

When using this product
• avoid contact with the eyes
• if contact occurs, rinse thoroughly with water

DIRECTIONS

clean the skin thoroughly before applying this product
• cover the entire affected area with a thin layer one to three
times daily
• because excessive drying of the skin may occur, start with
one application daily, then gradually increase to two or three
times daily if needed or as directed by a doctor
• if bothersome dryness or peeling occurs, reduce application
to once a day or every other day

INACTIVE INGREDIENTS

Aqua/Water/Eau, Sodium Methyl 2-Sulfolaurate, Disodium 2-Sulfolaurate, Disodium Laureth Sulfosuccinate, Lactococcus Ferment Lysate, Melaleuca Alternifolia (Tea Tree) Leaf Oil, Azelaic Acid, Morinda Citrifolia Extract, Glycyrrhiza Glabra (Licorice) Root Extract, Vaccinium Angustifolium (Blueberry) Fruit Extract, Zingiber Officinale (Ginger) Root Extract, Lactic Acid, Hydrolyzed Algin, Glycerin, Citric Acid, Phospholipids, Caprylyl Glycol, Sodium Chloride, Benzoic Acid, Sodium Hydroxide, Sodium Glycolate, Trisodium Dicarboxymethyl Alaninate, Butylene Glycol, Chlorphenesin, Sodium Benzoate, Ethylhexylglycerin, Phenoxyethanol

Questions or Comments?

1-844-545-1236

KEEP OUT OF THE REACH OF CHILDREN

Keep out of reach of children. If swallowed, get medical help - or contact a Poison Control Center right away.

Warnings and Precautions INDICATION AND USAGE SECTION ADDED DOSAGE & ADMINISTRATION SECTION

Warnings and Precautions added

INDICATION AND USAGE SECTION ADDED

DOSAGE & ADMINISTRATION SECTION